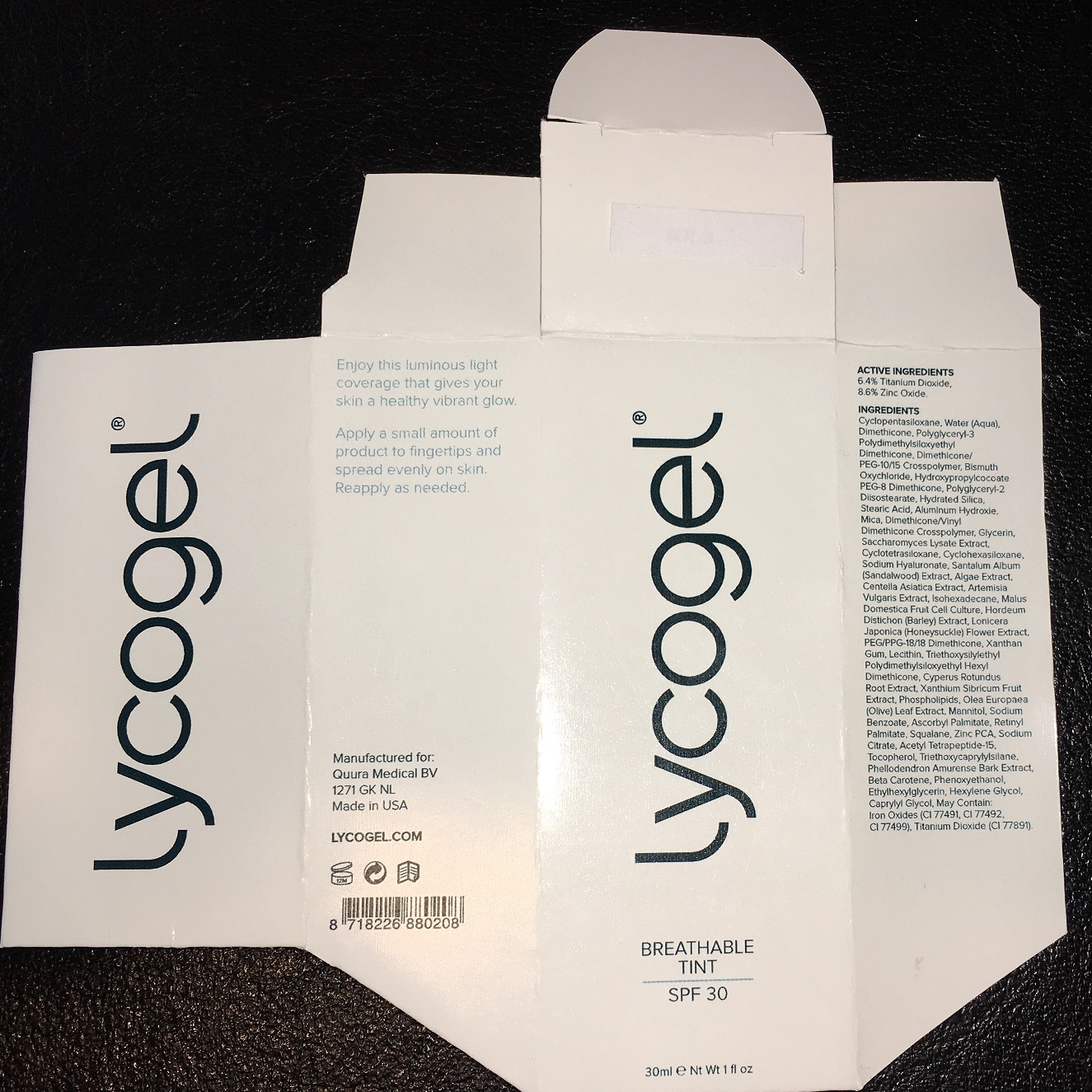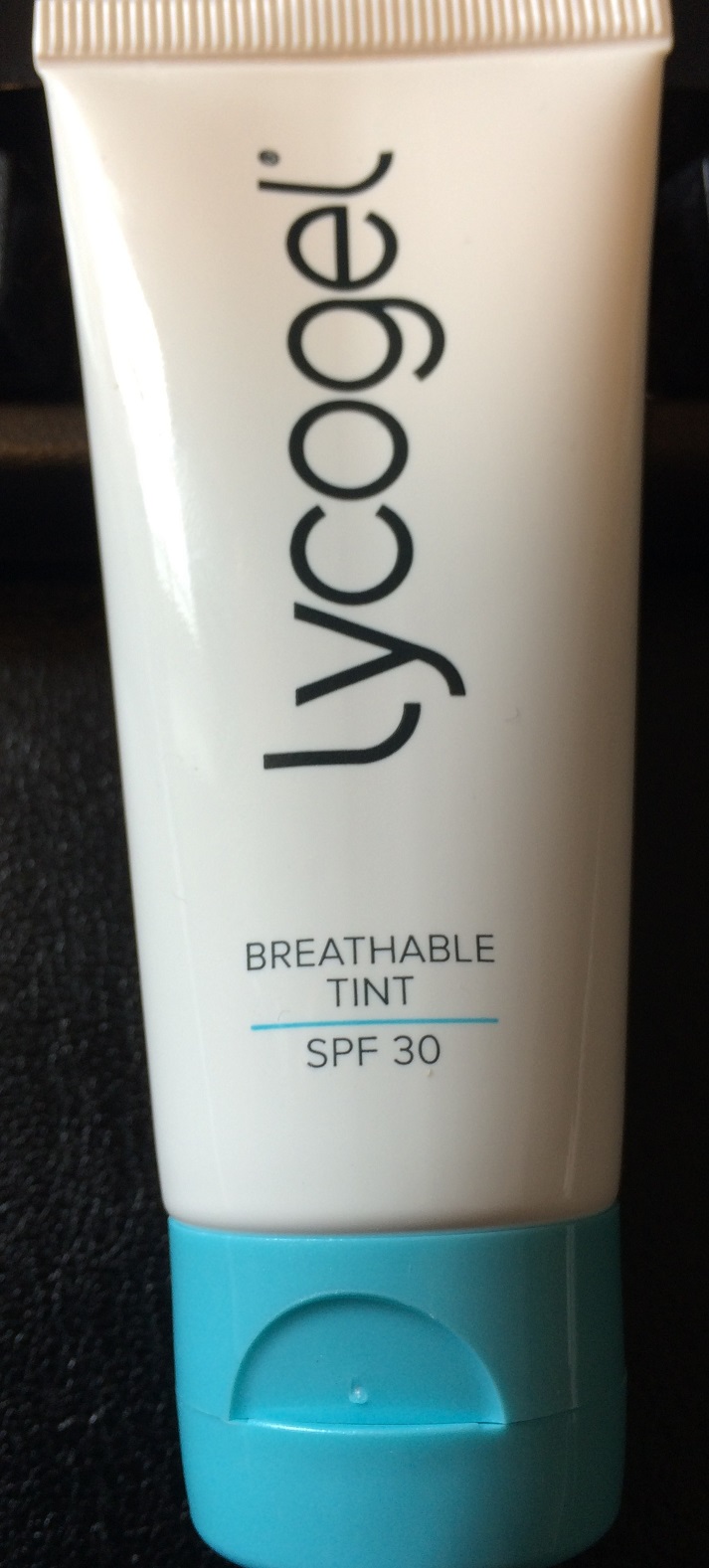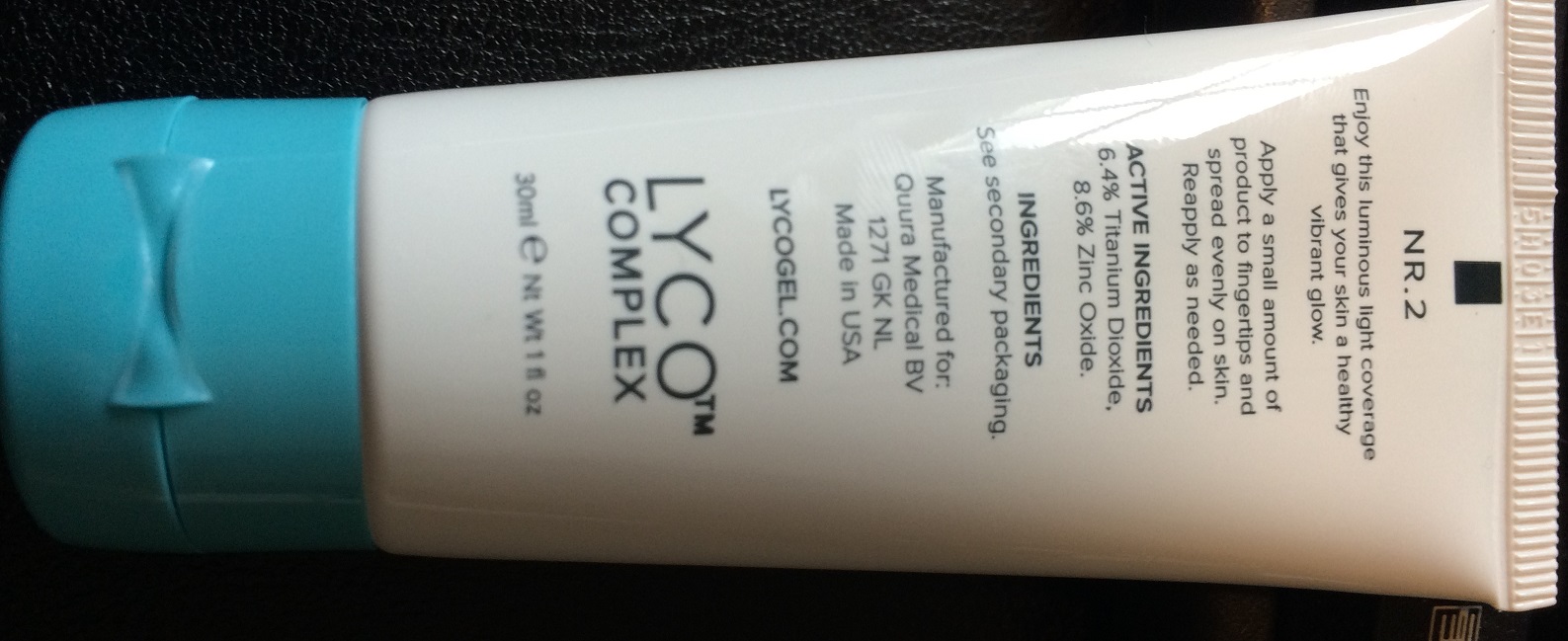 DRUG LABEL: Breathable Tint 1
NDC: 51790-300 | Form: CREAM
Manufacturer: Quura Medical B.V
Category: otc | Type: HUMAN OTC DRUG LABEL
Date: 20180109

ACTIVE INGREDIENTS: Zinc Oxide 86 mg/1 mL; Titanium Dioxide 64 mg/1 mL
INACTIVE INGREDIENTS: DIMETHICONE; BISMUTH OXYCHLORIDE; POLYGLYCERYL-3 POLYDIMETHYLSILOXYETHYL DIMETHICONE (4000 MPA.S); WATER; MICA; CETYL PEG/PPG-10/1 DIMETHICONE (HLB 4); HYDROXYPROPYLCOCOATE PEG-8 DIMETHICONE; POLYGLYCERYL-2 DIISOSTEARATE; STEARIC ACID; ALUMINUM HYDROXIDE; DIMETHICONE/VINYL DIMETHICONE CROSSPOLYMER (SOFT PARTICLE); GLYCERIN; SACCHAROMYCES LYSATE; CYCLOMETHICONE 6; HYALURONATE SODIUM; SANDALWOOD; CHLORELLA VULGARIS; CENTELLA ASIATICA; ARTEMISIA VULGARIS WHOLE; ISOHEXADECANE; Hydrated Silica; APPLE; BARLEY; LONICERA JAPONICA FLOWER; PEG/PPG-18/18 DIMETHICONE; XANTHAN GUM; LECITHIN, SOYBEAN; CYPERUS ROTUNDUS ROOT; XANTHIUM SIBIRICUM WHOLE; OMEGA-3 FATTY ACIDS; OLEA EUROPAEA LEAF; MANNITOL; SODIUM BENZOATE; ASCORBYL PALMITATE; VITAMIN A PALMITATE; SQUALANE; ZINC PIDOLATE; SODIUM CITRATE; ACETYL TETRAPEPTIDE-15; TOCOPHEROL; TRIETHOXYCAPRYLYLSILANE; PHELLODENDRON AMURENSE BARK; .BETA.-CAROTENE; Phenoxyethanol; ETHYLHEXYLGLYCERIN; HEXYLENE GLYCOL; CAPRYLYL GLYCOL; FERRIC OXIDE RED

Inactives

Cyclopentasiloxane,Zinc Oxide,Dimethicone,Titanium Dioxide,Bismuth Oxychloride,Polyglyceryl-3 Polydimethylsiloxyethyl Dimethicone
Water (Aqua),Mica,Dimethicone/PEG-10/15 Crosspolymer,Hydroxypropylcocoate PEG-8 Dimethicone,Polyglyceryl-2 Diisostearate, Stearic Acid,Aluminum Hydroxide,Dimethicone/Vinyl Dimethicone Crosspolymer,Glycerin,Saccharomyces Lysate Extract,Cyclotetrasiloxane,Cyclohexasiloxane,Sodium Hyaluronate,Santalum Album (Sandalwood) Extract,Algae Extract,Centella Asiatica Extract,Artemisia Vulgaris Extract,Isohexadecane,Hydrated Silica,Malus Domestica Fruit Cell Culture,Hordeum Distichon (Barley) Extract,Lonicera Japonica (Honeysuckle) Flower Extract,PEG/PPG-18/18 Dimethicone,Xanthan Gum,Lecithin,Triethoxysilylethyl Polydimethylsiloxyethyl Hexyl Dimethicone,Cyperus Rotundus Root Extract,Xanthium Sibiricum Fruit Extract,Phospholipids ,Olea Europaea (Olive) Leaf Extract,Mannitol,Sodium Benzoate,Ascorbyl Palmitate,Retinyl Palmitate,Squalane,Zinc PCA,Sodium Citrate,Acetyl Tetrapeptide-15,Tocopherol,Triethoxycaprylylsilane,Phellodendron Amurense Bark Extract,Beta-Carotene,Phenoxyethanol,Ethylhexylglycerin,Hexylene Glycol, Caprylyl Glycol,Iron Oxides (CI 77492),Iron Oxides (CI 77491),Iron Oxides (CI 77499),Titanium Dioxide (CI 77891)